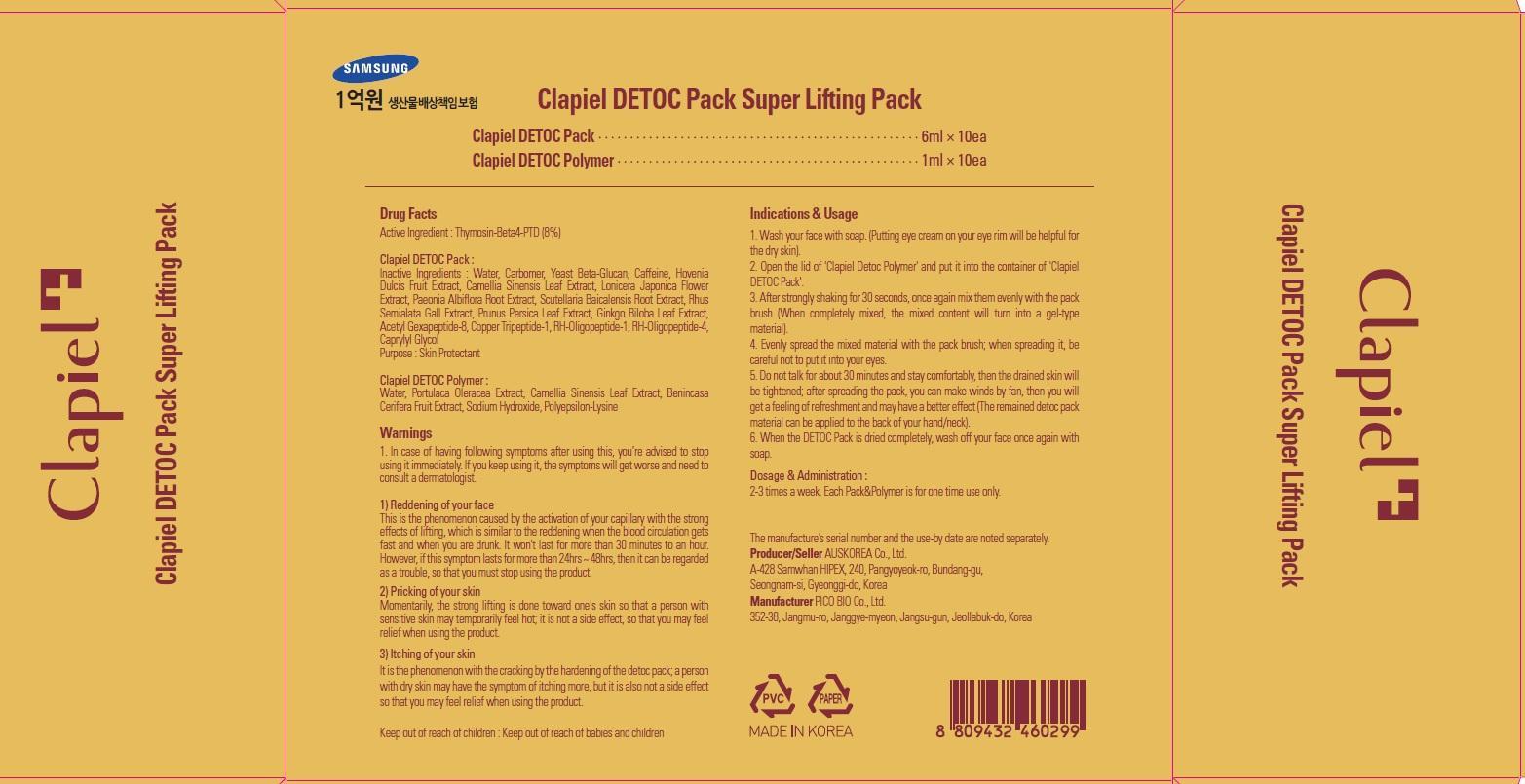 DRUG LABEL: CLAPIEL DETOC PACK SUPER LIFTING PACK
NDC: 69977-010 | Form: SOLUTION
Manufacturer: AUS KOREA CO., LTD.
Category: otc | Type: HUMAN OTC DRUG LABEL
Date: 20150723

ACTIVE INGREDIENTS: THIOREDOXIN 0.48 mg/10 1
INACTIVE INGREDIENTS: Water; Caffeine

ACTIVE INGREDIENT

Active Ingredient: Thymosin-Beta4-PTD(8%)

INACTIVE INGREDIENT

Clapiel DETOC Pack : Inactive Ingredients: Water, Carbomer, Yeast Beta-Glucan, Caffeine, Hovenia Dulcis Fruit Extract, Camellia Sinensis Leaf Extract, Lonicera Japonica Flower Extract, Paeonia Albiflora Root Extract, Scutellaria Baicalensis Root Extract, Rhus Semialata Gall Extract, Prunus Persica Leaf Extract, Ginkgo Biloba Leaf Extract, Acetyl Gexapeptide-8, Copper Tripeptide-1, RH-Oligopeptide-1, RH-Oligopeptide-4, Caprylyl Glycol Purpose: Skin Protectant

Clapiel DETOC Polymer : Water, Portulaca Oleracea Extract, Camellia Sinensis Leaf Extract, Benincasa Cerifera Fruit Extract, Sodium Hydroxide, Polyepsilon-Lysine

PURPOSE

PURPOSE: Skin Protectant

WARNINGS

Warnings: 1. In case of having following symptoms after using this, you’re advised to stop using it immediately. If you keep using it, the symptoms will get worse and need to consult a dermatologist.

1) Reddening of your face This is the phenomenon caused by the activation of your capillary with the strong effects of lifting, which is similar to the reddening when the blood circulation gets fast and when you are drunk. It won't last for more than 30 minutes to an hour. However, if this symptom lasts for more than 24hrs ~ 48hrs, then it can be regarded as a trouble, so that you must stop using the product.

2) Pricking of your skin Momentarily, the strong lifting is done toward one's skin so that a person with sensitive skin may temporarily feel hot; it is not a side effect, so that you may feel relief when using the product.

3) Itching of your skin It is the phenomenon with the cracking by the hardening of the detoc pack; a person with dry skin may have the symptom of itching more, but it is also not a side effect so that you may feel relief when using the product.

KEEP OUT OF REACH OF CHILDREN

Keep out of reach of babies and children

INDICATIONS & USAGE

Indications & Usage: 1. Wash your face with soap. (Putting eye cream on your eye rim will be helpful for the dry skin). 2. Open the lid of 'Clapiel Detoc Polymer' and put it into the container of 'Clapiel DETOC Pack'. 3. After strongly shaking for 30 seconds, once again mix them evenly with the pack brush (When completely mixed, the mixed content will turn into a gel-type material). 4. Evenly spread the mixed material with the pack brush; when spreading it, be careful not to put it into your eyes. 5. Do not talk for about 30 minutes and stay comfortably, then the drained skin will be tightened; after spreading the pack, you can make winds by fan, then you will get a feeling of refreshment and may have a better effect (The remained detoc pack material can be applied to the back of your hand/neck). 6. When the DETOC Pack is dried completely, wash off your face once again with soap.

DOSAGE & ADMINISTRATION

Dosage & Administration: 2-3 times a week. Each Pack&Polymer is for one time use only.